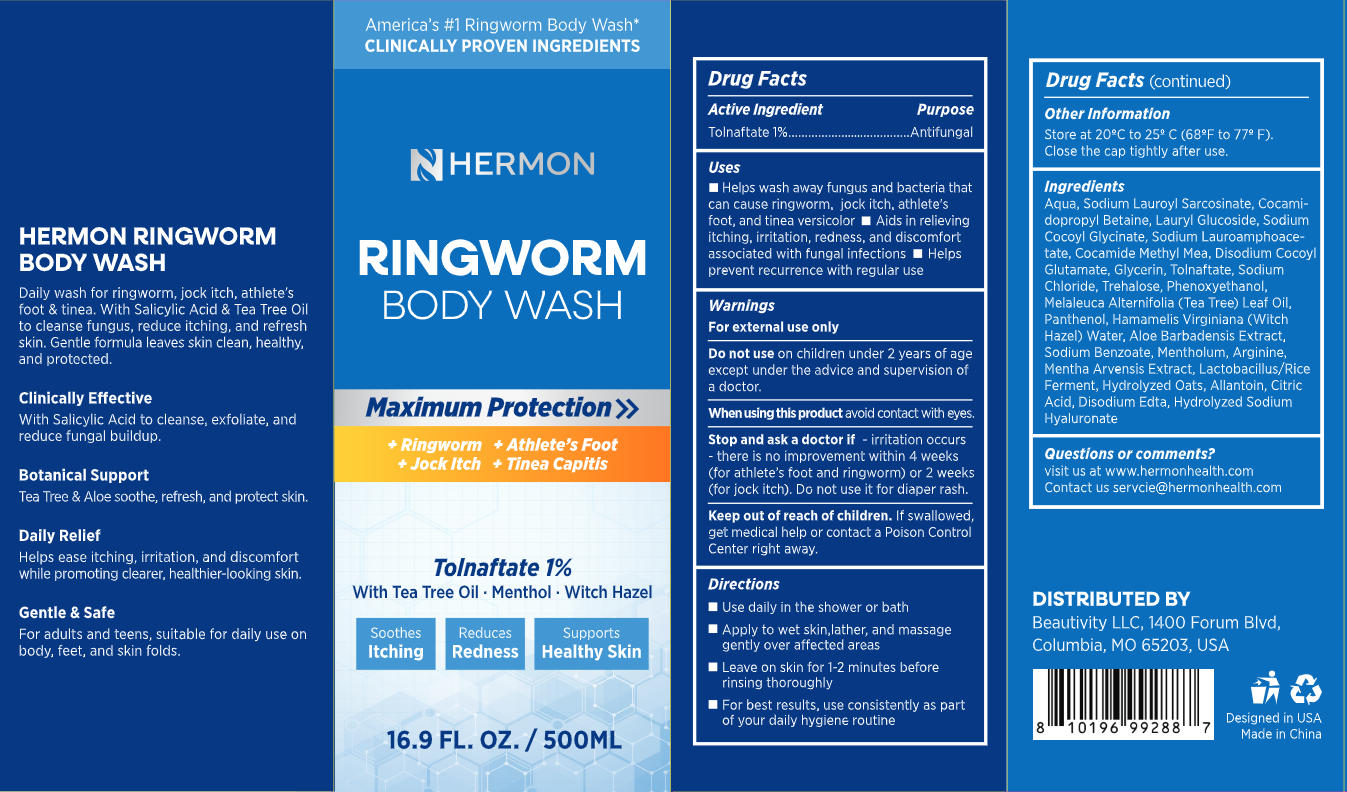 DRUG LABEL: Hermon Ringworm Treatment Body Wash
NDC: 85398-028 | Form: LIQUID
Manufacturer: Beautivity LLC
Category: otc | Type: HUMAN OTC DRUG LABEL
Date: 20260113

ACTIVE INGREDIENTS: TOLNAFTATE 5 g/500 g
INACTIVE INGREDIENTS: COCAMIDOPROPYL BETAINE; GLYCERIN; DISODIUM EDTA-COPPER; SODIUM CHLORIDE; PANTHENOL; SODIUM HYALURONATE; TREHALOSE; OAT; PHENOXYETHANOL; LAURYL GLUCOSIDE; LACTOBACILLUS; LEVOMENTHOL; AQUA; COCAMIDE METHYL MEA; MENTHA ARVENSIS LEAF OIL; ALLANTOIN; CITRIC ACID; SODIUM LAUROYL SARCOSINATE; SODIUM COCOYL GLYCINATE; ALOE BARBADENSIS LEAF JUICE; HAMAMELIS VIRGINIANA (WITCH HAZEL) LEAF WATER; ARGININE; SODIUM LAUROAMPHOACETATE; DISODIUM COCOYL GLUTAMATE; MELALEUCA ALTERNIFOLIA (TEA TREE) LEAF OIL; SODIUM BENZOATE

Initial Drug Listing - Hermon Ringworm Treatment Body Wash

ACTIVE INGREDIENT

Tolnaftate 1%

PURPOSE

Antifungal

DOSAGE AND ADMINISTRATION

- Helps wash away fungus and bacteria that can cause ringworm, jock itch,athlete's foot, and tinea versicolor
- Aids in relievingitching,irritation, redness, and discomfort associated with fungal infections
- Helps prevent recurrence with regular use

WARNINGS

For external use only

DO NOT USE

on children under 2 years of age except under the advice and supervision of a doctor.

WHEN USING

avoid contact with eyes.

ASK DOCTOR

irritation occurs-there is no improvement within 4 weeks(for athlete's foot and ringworm) or 2 weeks(for jock itch). Do not use it for diaper rash.

KEEP OUT OF REACH OF CHILDREN

If swallowed,get medical help or contact a Poison Control Center right away.

INDICATIONS AND USAGE

- Use daily in the shower or bath
- Apply to wet skin,lather, and massage gently over affected areas
- Leave on skin for 1-2 minutes before rinsing thoroughly
- For best results, use consistently as partof your daily hygiene routine

OTHER SAFETY INFORMATION

Store at 20Cto 25C(68F to 77F).
Close the cap tightly after use.

INACTIVE INGREDIENT

Aqua, Sodium Lauroyl Sarcosinate, Cocamidopropyl Betaine, Lauryl Glucoside, Sodium Cocoyl Glycinate, Sodium Lauroamphoacetate, Cocamide MethyI Mea, Disodium Cocoyl Glutamate, Glycerin, Sodium Chloride, Trehalose, Phenoxyethanol,Melaleuca Alternifolia (Tea Tree) Leaf Oil,Panthenol, Hamamelis Virginiana (WitchHazel) Water, Aloe Barbadensis Extract, Sodium Benzoate, Mentholum, Arginine,Mentha Arvensis Extract, Lactobacillus/RiceFerment, Hydrolyzed Oats, Allantoin, Citric Acid, Disodium Edta, Hydrolyzed Sodium Hyaluronate

QUESTIONS

Visit us at www.hermonhealth.com

Contact us servcie@hermonhealth.com